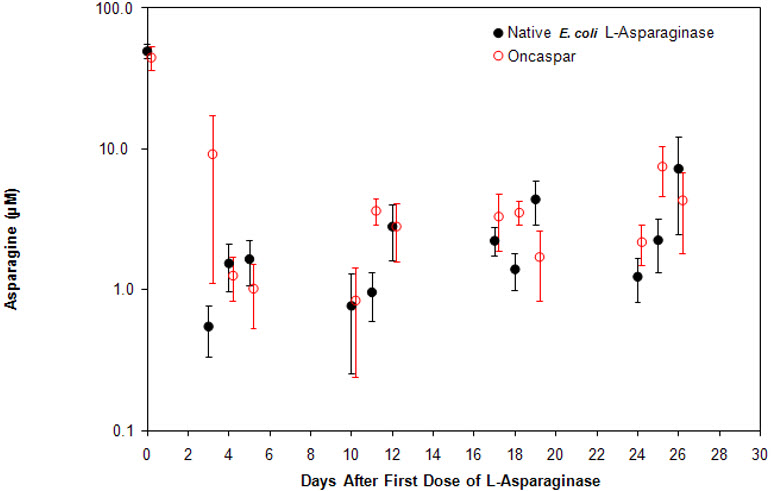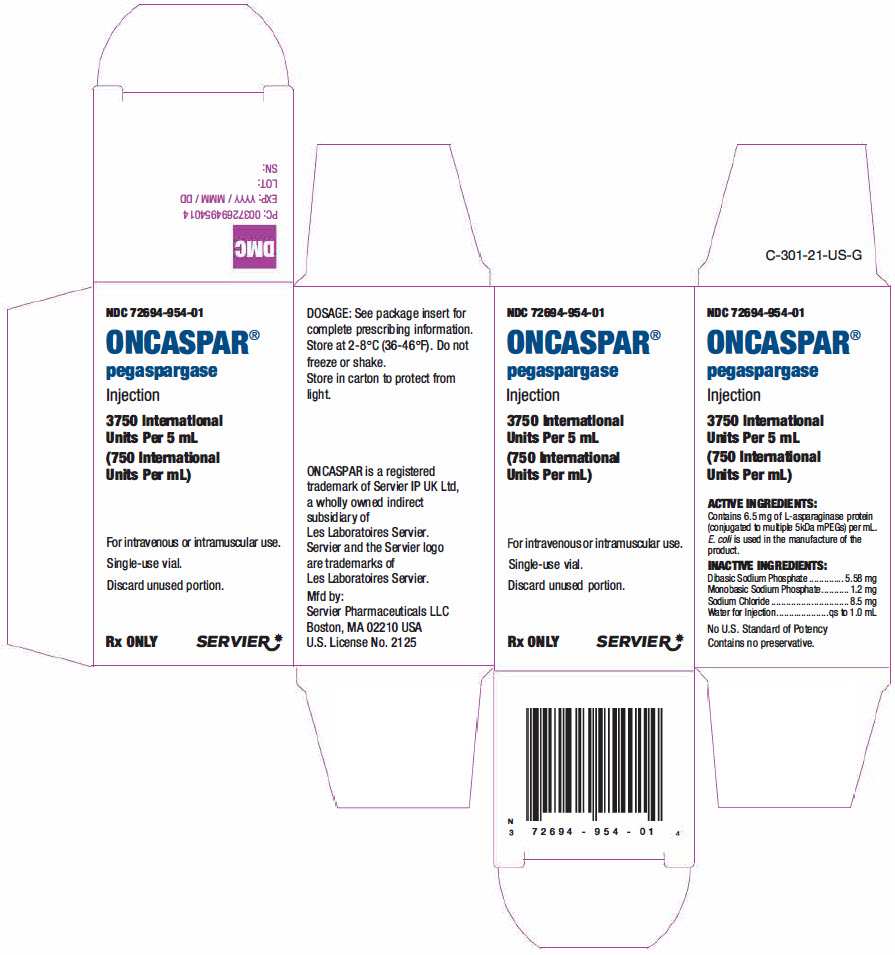 DRUG LABEL: ONCASPAR
NDC: 72694-954 | Form: INJECTION, SOLUTION
Manufacturer: Servier Pharmaceuticals LLC
Category: prescription | Type: HUMAN PRESCRIPTION DRUG LABEL
Date: 20241007

ACTIVE INGREDIENTS: PEGASPARGASE 750 [iU]/1 mL
INACTIVE INGREDIENTS: SODIUM PHOSPHATE, MONOBASIC, DIHYDRATE; SODIUM PHOSPHATE, DIBASIC, UNSPECIFIED FORM; SODIUM CHLORIDE; WATER

HIGHLIGHTS OF PRESCRIBING INFORMATION

These highlights do not include all the information needed to use ONCASPAR safely and effectively. See full prescribing information for ONCASPAR.
ONCASPAR (pegaspargase) injection, for intramuscular or intravenous use
Initial U.S. Approval: 1994

RECENT MAJOR CHANGES

Warnings and Precautions (5.6) | 3/2024

1 INDICATIONS AND USAGE

ONCASPAR is an asparagine specific enzyme indicated as a component of a multi-agent chemotherapeutic regimen for treatment of pediatric and adult patients with:

- First-line acute lymphoblastic leukemia (1.1)
- Acute lymphoblastic leukemia and hypersensitivity to asparaginase (1.2)

2 DOSAGE AND ADMINISTRATION

- Administered intramuscularly or intravenously no more frequently than every 14 days. (2.1)
- Patients ages 21 years and younger: 2,500 International Units/m^2. (2.1)
- Patients ages over 21 years: 2,000 International Units/m^2. (2.1)
- For intramuscular administration, limit the volume at a single injection site to 2 mL; if greater than 2 mL, use multiple injection sites. (2.3)
- For intravenous administration, give over a period of 1 to 2 hours in 100 mL of 0.9% Sodium Chloride Injection, USP or 5% Dextrose Injection, USP through an infusion that is already running. (2.3)
- Do not administer ONCASPAR if drug has been frozen, stored at room temperature for more than 48 hours, or shaken or vigorously agitated. (16)

3 DOSAGE FORMS AND STRENGTHS

- Injection: 3,750 International Units/5 mL (750 International Units/mL) solution in a single-dose vial. (3)

4 CONTRAINDICATIONS

- History of serious hypersensitivity reactions to ONCASPAR. (4)
- History of serious thrombosis with prior L-asparaginase therapy. (4)
- History of pancreatitis with prior L-asparaginase therapy. (4)
- History of serious hemorrhagic events with prior L-asparaginase therapy. (4)
- Severe hepatic impairment. (4)

5 WARNINGS AND PRECAUTIONS

- Anaphylaxis or serious hypersensitivity reactions: Observe patients for 1 hour after administration. Discontinue ONCASPAR in patients with serious hypersensitivity reactions. (5.1)
- Thrombosis: Discontinue ONCASPAR in patients with serious thrombotic events. (5.2)
- Pancreatitis: Evaluate patients with abdominal pain for pancreatitis. Discontinue ONCASPAR in patients with pancreatitis. (5.3)
- Glucose intolerance: Monitor serum glucose. (5.4)
- Hemorrhage: Discontinue ONCASPAR for severe or life-threatening hemorrhage. Evaluate for etiology and treat. (5.5)
- Hepatotoxicity, including hepatic veno-occlusive disease (VOD): Monitor for toxicity through recovery from cycle. Discontinue ONCASPAR for severe liver toxicity. (5.6)

6 ADVERSE REACTIONS

The most common (>5%) grade >3 adverse reactions with ONCASPAR are hypoalbuminemia, elevated transaminase, febrile neutropenia, hypertriglyceridemia, hyperglycemia, bilirubin increased, pancreatitis, abnormal clotting studies, embolic and thrombotic events, hypersensitivity, sepsis, and infections. (6.1)

To report SUSPECTED ADVERSE REACTIONS, contact Servier Pharmaceuticals, at 1-800-807-6124 or FDA at 1-800-FDA-1088 or www.fda.gov/medwatch.

8 USE IN SPECIFIC POPULATIONS

Lactation: Advise not to breastfeed. (8.2)

FULL PRESCRIBING INFORMATION

1 INDICATIONS AND USAGE

1.1 First Line Acute Lymphoblastic Leukemia (ALL)

ONCASPAR® is indicated as a component of a multi-agent chemotherapeutic regimen for the first-line treatment of pediatric and adult patients with ALL.

1.2 Acute Lymphoblastic Leukemia and Hypersensitivity to Asparaginase

ONCASPAR is indicated as a component of a multi-agent chemotherapeutic regimen for the treatment of pediatric and adult patients with ALL and hypersensitivity to native forms of L-asparaginase.

2 DOSAGE AND ADMINISTRATION

2.1 Recommended Dosage

Patients 21 Years of Age or Younger

The recommended dose of ONCASPAR for patients up to and including 21 years of age is 2,500 International Units/m^2 intramuscularly or intravenously no more frequently than every 14 days.

Patients More Than 21 Years of Age

The recommended dose of ONCASPAR for adult patients more than 21 years of age is 2,000 International Units/m^2 intramuscularly or intravenously no more frequently than every 14 days.

2.2 Recommended Premedication

Premedicate patients with acetaminophen, an H-1 receptor blocker (such as diphenhydramine), and an H-2 receptor blocker (such as famotidine) 30-60 minutes prior to administration of ONCASPAR to decrease the risk and severity of both infusion and hypersensitivity reactions [see Warnings and Precautions (5.1)].

2.3 Recommended Monitoring and Dosage Modifications for Adverse Reactions

Monitor patients at least weekly, with bilirubin, transaminases, glucose and clinical examinations until recovery from the cycle of therapy. If an adverse reaction should occur, modify treatment according to Table 1.

Table 1. Dosage Modifications
Adverse Reaction | Severity [Grade 1 is mild, grade 2 is moderate, grade 3 is severe, and grade 4 is life-threatening.] | Action
Infusion Reaction/Hypersensitivity Reaction [see Warnings and Precautions (5.1)] | Grade 1 | - Reduce the infusion rate by 50%
Infusion Reaction/Hypersensitivity Reaction [see Warnings and Precautions (5.1)] | Grade 2 | - Interrupt the infusion of ONCASPAR - Treat the symptoms - When symptoms resolve, resume the infusion and reduce the infusion rate by 50%
Infusion Reaction/Hypersensitivity Reaction [see Warnings and Precautions (5.1)] | Grade 3 to 4 | - Discontinue ONCASPAR permanently
Thrombosis [see Warnings and Precautions (5.2)] | Uncomplicated deep vein thrombosis | - Hold ONCASPAR - Treat with appropriate antithrombotic therapy - Upon resolution of symptoms consider resuming ONCASPAR, while continuing antithrombotic therapy
Thrombosis [see Warnings and Precautions (5.2)] | Severe or life-threatening thrombosis | - Discontinue ONCASPAR permanently - Treat with appropriate antithrombotic therapy
Pancreatitis [see Warnings and Precautions (5.3)] | Grades 3 to 4 | - Hold ONCASPAR for elevations in lipase or amylase >3 × ULN until enzyme levels stabilize or are declining - Discontinue ONCASPAR permanently if clinical pancreatitis is confirmed
Hemorrhage [see Warnings and Precautions (5.5)] | Grade 3 to 4 | - Hold ONCASPAR - Evaluate for coagulopathy and consider clotting factor replacement as needed - Resume ONCASPAR with the next scheduled dose if bleeding is controlled
Hepatotoxicity [see Warnings and Precautions (5.6)] | Total bilirubin more than 3 times to no more than 10 times the ULN | - Hold ONCASPAR until total bilirubin is ≤1.5 times the ULN
Hepatotoxicity [see Warnings and Precautions (5.6)] | Total bilirubin more than 10 times the ULN | - Discontinue ONCASPAR and do not make up for missed doses

2.4 Preparation and Administration

Administer ONCASPAR in a healthcare setting with appropriate medical support and resuscitation equipment to manage hypersensitivity reactions, should they occur [see Warnings and Precautions (5.1)].

ONCASPAR is a clear and colorless solution. Visually inspect parenteral drug products for particulate matter, cloudiness, or discoloration prior to administration. If any of these are present, discard the vial.

When ONCASPAR is administered intramuscularly:

- Limit the volume at a single injection site to 2 mL.
- If the volume to be administered is greater than 2 mL, use multiple injection sites.

When ONCASPAR is administered intravenously:

- Dilute ONCASPAR with 100 mL of 0.9% Sodium Chloride Injection, USP or 5% Dextrose Injection, USP, using aseptic technique.
- After dilution, administer immediately into a running infusion of either 0.9% Sodium Chloride, USP or 5% Dextrose Injection, USP, respectively.
- Administer over a period of 1-2 hours.
- Do not infuse other drugs through the same intravenous line during administration of ONCASPAR.
- The diluted solution should be used immediately. If immediate use is not possible, the diluted solution should be stored refrigerated at 2°C to 8°C (36°F to 46°F) for up to 48 hours. Protect infusion bags from direct sunlight.

ONCASPAR does not contain a preservative. Use only one dose per vial; discard unused product.

3 DOSAGE FORMS AND STRENGTHS

Injection: 3,750 International Units/5 mL (750 International Units/mL) clear, colorless solution in a single-dose vial.

4 CONTRAINDICATIONS

ONCASPAR is contraindicated in patients with a:

- History of serious hypersensitivity reactions, including anaphylaxis, to ONCASPAR or to any of the excipients [see Warnings and Precautions (5.1)].
- History of serious thrombosis with prior L-asparaginase therapy [see Warnings and Precautions (5.2)].
- History of pancreatitis, including pancreatitis related to prior L-asparaginase therapy [see Warnings and Precautions (5.3)].
- History of serious hemorrhagic events with prior L-asparaginase therapy [see Warnings and Precautions (5.5)].
- Severe hepatic impairment [see Warnings and Precautions (5.6)].

5 WARNINGS AND PRECAUTIONS

5.1 Anaphylaxis and Serious Hypersensitivity Reactions

Anaphylaxis and serious hypersensitivity reactions can occur in patients receiving ONCASPAR. The risk of serious hypersensitivity reactions is higher in patients with known hypersensitivity to (E.) coli derived L-asparaginase formulations. Other hypersensitivity reactions can include angioedema, lip swelling, eye swelling, erythema, blood pressure decreased, bronchospasm, dyspnea, pruritus, and rash [see Adverse Reactions (6.1)].

Premedicate patients 30-60 minutes prior to administration of ONCASPAR. [see Dosage and Administration (2.2)]. Observe patients for 1 hour after administration of ONCASPAR in a setting with resuscitation equipment and other agents necessary to treat anaphylaxis (for example, epinephrine, oxygen, intravenous steroids, antihistamines) [see Dosage and Administration (2.4)]. Discontinue ONCASPAR in patients with serious hypersensitivity reactions.

5.2 Thrombosis

Serious thrombotic events, including sagittal sinus thrombosis can occur in patients receiving ONCASPAR [see Adverse Reactions (6.1)]. Discontinue ONCASPAR in patients with serious thrombotic events [see Dosage and Administration (2.3)].

5.3 Pancreatitis

Pancreatitis can occur in patients receiving ONCASPAR. Hemorrhagic or necrotizing pancreatitis with fatal outcomes have been reported [see Adverse Reactions (6.1)]. Inform patients of the signs and symptoms of pancreatitis, which, if left untreated, could be fatal. Assess serum amylase and/or lipase levels to confirm early signs of pancreatic inflammation. Discontinue ONCASPAR in patients where pancreatitis is suspected. If pancreatitis is confirmed, do not resume ONCASPAR [see Dosage and Administration (2.3)].

5.4 Glucose Intolerance

Glucose intolerance can occur in patients receiving ONCASPAR [see Adverse Reactions (6.1)]. In some cases, glucose intolerance is irreversible. Monitor serum glucose [see Dosage and Administration (2.3)].

5.5 Hemorrhage

Increased prothrombin time, increased partial thromboplastin time, and hypofibrinogenemia can occur in patients receiving ONCASPAR [see Adverse Reactions (6.1)]. Evaluate patients with signs and symptoms of hemorrhage with coagulation parameters including PT, PTT, fibrinogen. Consider appropriate replacement therapy in patients with severe or symptomatic coagulopathy. Discontinue ONCASPAR for severe or life-threatening hemorrhage [see Dosage and Administration (2.3)].

5.6 Hepatotoxicity, Including Hepatic Veno-Occlusive Disease

Hepatotoxicity, including severe, life-threatening, and potentially fatal cases of hepatic veno-occlusive disease (VOD), have been observed in patients treated with ONCASPAR in combination with standard chemotherapy, including during the induction phase of multiphase chemotherapy [see Adverse Reactions (6)]. Do not administer ONCASPAR to patients with severe hepatic impairment [see Contraindications (4)].

Evaluate bilirubin and transaminases prior to each dose of ONCASPAR and at least weekly, during cycles of treatment that include ONCASPAR, through 6 weeks after the last dose of ONCASPAR. Monitor frequently for signs and symptoms of hepatic VOD, which may include rapid weight gain, fluid retention with ascites, hepatomegaly (which may be painful), and rapid increase of bilirubin. For patients who develop abnormal liver tests after ONCASPAR, more frequent monitoring for liver test abnormalities and clinical signs and symptoms of VOD is recommended. In the event of serious liver toxicity, including VOD, discontinue treatment with ONCASPAR and provide supportive care [see Dosage and Administration (2.3)].

6 ADVERSE REACTIONS

The following clinically significant adverse reactions are described elsewhere in the labeling:

- Anaphylaxis and serious hypersensitivity reactions [see Warnings and Precautions (5.1)]
- Thrombosis [see Warnings and Precautions (5.2)]
- Pancreatitis [see Warnings and Precautions (5.3)]
- Glucose intolerance [see Warnings and Precautions (5.4)]
- Hemorrhage [see Warnings and Precautions (5.5)]
- Hepatotoxicity, including VOD [see Warnings and Precautions (5.6)]

6.1 Clinical Trials Experience

Because clinical trials are conducted under widely varying conditions, the adverse reaction rates observed cannot be directly compared to rates in other clinical trials and may not reflect the rates observed in clinical practice.

The most common grade 3 and 4 adverse reactions (>5%) included: hypoalbuminemia, elevated transaminase, febrile neutropenia, hypertriglyceridemia, hyperglycemia, bilirubin increased, pancreatitis, abnormal clotting studies, embolic and thrombotic events, hypersensitivity, sepsis, and infections.

First-Line Treatment of Acute Lymphoblastic Leukemia (ALL)

Study CCG-1962 was a randomized (1:1), active controlled study that enrolled 118 patients, with a median age of 4.7 years (1.1-9.9 years), of whom 54% were males and 65% White, 14% Hispanic, 8% Black, 8% Asian, and 6% other race. Of the 59 patients in Study 1 who were randomized to ONCASPAR, 48 patients (81%) received all 3 planned doses of ONCASPAR, 6 (10%) received 2 doses, 4 (7%) received 1 dose, and 1 patient (2%) did not receive the assigned treatment.

In Study CCG-1962, detailed safety information was collected for pre-specified adverse reactions identified as asparaginase induced adverse reactions and for grade 3 and 4 nonhematologic adverse reactions according to the Children's Cancer Group (CCG) Toxicity and Complication Criteria. The per-patient incidence, by treatment arm, for these selected adverse reactions occurring at a severity of grade 3 or 4 are presented in Table 2:

Table 2. Incidence of Selected Grades 3 and 4 Adverse Reactions in Study CCG-1962
 | ONCASPAR (n=58) | Native E. coli L-Asparaginase (n=59)
Infection | 3 (5%) | 3 (5%)
Abnormal Liver Tests | 3 (5%) | 5 (8%)
Elevated Transaminases [Aspartate aminotransferase, alanine aminotransferase.] | 2 (3%) | 4 (7%)
Hyperbilirubinemia | 1 (2%) | 1 (2%)
Hyperglycemia | 3 (5%) | 2 (3%)
Central Nervous System Thrombosis | 2 (3%) | 2 (3%)
Coagulopathy [Prolonged prothrombin time or partial thromboplastin time; or hypofibrinogenemia.] | 1 (2%) | 3 (5%)
Pancreatitis | 1 (2%) | 1 (2%)
Allergic Reactions to Asparaginase | 1 (2%) | 0

The safety of ONCASPAR was investigated in Study DFCI 11-001, an open label, randomized, active-controlled multicenter clinical trial that included 119 children and adolescents with newly diagnosed ALL or lymphoblastic lymphoma treated with ONCASPAR in combination with the Dana Farber Cancer Institute (DFCI) ALL Consortium backbone therapy. The median age on enrollment was 4 years (range, 1-18 years). The majority of patients were male (60%) and white (75%). Most patients were considered standard risk ALL (59%) and had B-cell lineage ALL (87%).

The median number of doses of ONCASPAR during the study was 16 doses (one dose during induction therapy then administered every two weeks during post induction therapy). The median duration of exposure to ONCASPAR was 8 months. Table 3 summarizes the incidence of selected Grades ≥3 adverse reactions that occurred in 2 or more patients receiving ONCASPAR. Because not all grade 1 and 2 adverse reactions were collected prospectively, only grade 3 and 4 adverse reactions are presented in Table 3.

Table 3. Incidence of Selected Grades ≥3 Adverse Reactions in Patients Receiving ONCASPAR With Multi-Agent Chemotherapy in Study DFCI 11-001
Adverse Reaction [Grouped terms: Elevated transaminase: Alanine aminotransferase increased, Aspartate aminotransferase increased; Pancreatitis: Amylase increased, Lipase increased, Pancreatic necrosis, Pancreatitis, Pancreatitis relapsing; Bilirubin increased: Bilirubin conjugated increased, Blood bilirubin increased; Abnormal clotting studies: Activated partial thromboplastin time prolonged, Blood fibrinogen decreased; Febrile neutropenia: Febrile neutropenia; Embolic and thrombotic events: Embolism, Pulmonary embolism, Thrombosis in device, Venous thrombosis, Venous thrombosis limb; Hypersensitivity: Hypersensitivity, Anaphylactic reaction, Drug hypersensitivity; Pneumonia: Lung infection, Pneumonia, Pneumonitis; Sepsis: Bacterial sepsis, Sepsis; Diarrhea: Colitis, Diarrhea, Enterocolitis, Neutropenic colitis; Hemorrhages SMQ (excludes laboratory terms): Disseminated intravascular coagulation, Epistaxis, Hematoma, Hemorrhage intracranial, Melena, Esophageal ulcer hemorrhage, Small intestinal hemorrhage, Upper gastrointestinal hemorrhage; Fungal infection: Fungal infection, Hepatic infection fungal, Respiratory tract infection fungal, Splenic infection fungal, Systemic candida.] | ONCASPAR 2500 IU/m^2 N=119 Grade ≥3 [Grading is based on the Common Terminology Criteria for Adverse Events (CTCAE) v4.0.] n (%)
Elevated transaminase | 79 (66)
Febrile neutropenia | 48 (40)
Hypertriglyceridemia | 36 (30)
Hypoalbuminemia | 33 (28)
Bilirubin increased | 30 (25)
Hyperglycemia | 29 (24)
Pancreatitis | 29 (24)
Abnormal clotting studies | 25 (21)
Embolic and thrombotic events | 10 (8)
Hypersensitivity | 8 (7)
Pneumonia | 8 (7)
Sepsis | 7 (6)
Diarrhea | 6 (5)
Hemorrhages | 5 (4)
Fungal Infection | 3 (3)

Previously Treated ALL

Adverse reaction information was obtained from 5 clinical trials that enrolled a total of 174 patients with relapsed ALL who received ONCASPAR as a single agent or in combination with multi-agent chemotherapy [see Clinical Studies (14.2)]. The toxicity profile of ONCASPAR in patients with previously treated relapsed ALL is similar to that reported above with the exception of clinical allergic reactions (see Table 3).

The most common adverse reactions of ONCASPAR were clinical allergic reactions, elevated transaminases, hyperbilirubinemia, and coagulopathies. The most common serious adverse events due to ONCASPAR treatment were thrombosis (4%), hyperglycemia requiring insulin therapy (3%), and pancreatitis (1%).

Allergic Reactions

Allergic reactions include the following: bronchospasm, hypotension, laryngeal edema, local erythema or swelling, systemic rash, and urticaria.

Among 58 ONCASPAR-treated patients enrolled in Study CCG-1962, clinical allergic reactions were reported in 2 patients (3%). One patient experienced a grade 1 allergic reaction and the other grade 3 hives; both occurred during the first delayed intensification phase of the study (see Table 4).

Among 62 patients with relapsed ALL and prior hypersensitivity reactions to asparaginase, 35 patients (56%) had a history of clinical allergic reactions to native Escherichia (E.) coli L-asparaginase, and 27 patients (44%) had a history of clinical allergic reactions to both native E. coli and native Erwinia L-asparaginase. Twenty (32%) of these 62 patients experienced clinical allergic reactions to ONCASPAR (see Table 4).

Among 112 patients with relapsed ALL with no prior hypersensitivity reactions to asparaginase, 11 patients (10%) experienced clinical allergic reactions to ONCASPAR (see Table 4).

Table 4. Incidence of Clinical Allergic Reactions, Overall and by Severity Grade
Patient Status | Toxicity Grade, n (%) |  |  |  | Total
Patient Status | 1 | 2 | 3 | 4 | Total
Previously Hypersensitive Patients (n=62) | 7 (11) | 8 (13) | 4 (6) | 1 (2) | 20 (32)
Non-Hypersensitive Patients (n=112) | 5 (4) | 4 (4) | 1 (1) | 1 (1) | 11 (10)
First Line (n=58) | 1 (2) | 0 | 1 (2) | 0 | 2 (3)

6.2 Immunogenicity

As with all therapeutic proteins, there is a potential for immunogenicity. The detection of antibody formation is highly dependent on the sensitivity and specificity of the assay. Additionally, the observed incidence of antibody (including neutralizing antibody) positivity in an assay may be influenced by several factors, including assay methodology, sample handling, timing of sample collection, concomitant medications, and underlying disease. For these reasons, comparison of the incidence of antibodies in the studies described below with the incidence of antibodies in other studies or to other asparaginase products may be misleading.

In Study CCG-1962, ONCASPAR treated patients were assessed for evidence of binding antibodies using an enzyme-linked immunosorbent assay (ELISA) method. The incidence of protocol-specified "high-titer" antibody formation was 2% in Induction (n=48), 10% in Delayed Intensification 1 (n=50), and 11% in Delayed Intensification 2 (n=44). In study CCG-1962, there is insufficient information to determine whether the development of antibodies is associated with an increased risk of clinical allergic reactions or altered pharmacokinetics (i.e., loss of asparaginase activity).

In Study DFCI 11-001, of the 100 evaluable patients treated with ONCASPAR, 19 (19%) patients developed anti-drug antibodies (ADA) during treatment; 18 of these 19 patients were positive for anti-PEG antibodies. The presence of ADA correlated with the occurrence of hypersensitivity reactions. There is insufficient information to determine whether the development of antibodies is associated with altered pharmacokinetics (i.e., loss of asparaginase activity).

6.3 Postmarketing Experience

The following adverse reactions have been identified during post-approval use of ONCASPAR. Because these reactions are reported voluntarily from a population of uncertain size, it is not always possible to reliably estimate their frequency or establish a causal relationship to drug exposure.

Blood and lymphatic system disorders: Coagulopathy.

Gastrointestinal disorders: Hepatic impairment, pancreatic cyst, pancreatitis.

Hepatic: Veno-occlusive disease.

Immune system disorders: Anaphylactic shock, hypersensitivity reaction.

Investigations: Blood cholesterol increased.

Metabolism and nutrition disorders: Hyperglycemia, hyperammonemia.

Musculoskeletal and connective tissue disorders: Osteonecrosis.

Vascular disorders: Hemorrhage including central nervous system hemorrhage, thrombosis including superior sagittal sinus thrombosis.

7 DRUG INTERACTIONS

7.1 Glucocorticoids

Pegaspargase may increase the risk of glucocorticoid-induced toxicities, including osteonecrosis through a potential increase in exposure of dexamethasone [see Adverse Reactions (6.3)].

8 USE IN SPECIFIC POPULATIONS

8.1 Pregnancy

Risk summary

Based on published literature studies with L-asparaginase in pregnant animals, ONCASPAR can cause fetal harm when administered to a pregnant woman. There are no available data on ONCASPAR use in pregnant women to evaluate for a drug-associated risk of major birth defects, miscarriage, or adverse maternal or fetal outcomes. Published literature studies in pregnant animals suggest asparagine depletion may cause harm to the animal offspring (see Data). Advise pregnant women of the potential risk to a fetus. In the U.S. general population, the estimated background risks of major birth defects and miscarriage in clinically recognized pregnancies are 2 to 4% and 15 to 20%, respectively.

Data

Animal Data

Animal reproduction studies have not been conducted with ONCASPAR to evaluate its effect on reproduction and fetal development. Published literature studies in which pregnant rabbits were administered L-asparaginase or pregnant rats were deprived of dietary asparagine suggested harm to the animal offspring.

8.2 Lactation

Risk summary

There are no data on the presence of pegaspargase in human milk, the effects on the breastfed child, or the effects on milk production. Because of the potential for adverse reactions in the breastfed child, advise women not to breastfeed during treatment with ONCASPAR and for 1 month after the last dose.

8.3 Females and Males of Reproductive Potential

ONCASPAR can cause fetal harm when administered to a pregnant woman [see Use in Specific Populations (8.1)].

Pregnancy

Pregnancy testing is recommended in females of reproductive potential prior to initiating ONCASPAR.

Contraception

Advise females of reproductive potential to use effective non-hormonal contraceptive methods during treatment with ONCASPAR and for 3 months after the last dose.

8.4 Pediatric Use

The safety and effectiveness of ONCASPAR in the treatment of ALL have been established in pediatric patients. Use of ONCASPAR in these age groups is supported by evidence of efficacy as first-line treatment from one adequate and well-controlled trial, and evidence of efficacy for treatment of patients with hypersensitivity to asparaginase from four adequate and well-controlled trials [see Clinical Studies (14.1)], and safety data from 7 total trials. The pediatric patients treated with ONCASPAR 2,500 International Units/m^2 on these trials included 26 infants (1 month to <2 years old), 165 children (2 years to <12 years old), and 39 adolescents (12 to 17 years old).

8.5 Geriatric Use

Clinical studies of ONCASPAR did not include sufficient numbers of subjects aged 65 years and older to determine whether they respond differently than younger subjects.

10 OVERDOSAGE

Three patients received 10,000 International Units/m^2 of ONCASPAR as an intravenous infusion. One patient experienced a slight increase in liver enzymes. A second patient developed a rash 10 minutes after the start of the infusion, which was controlled with the administration of an antihistamine and by slowing down the infusion rate. A third patient did not experience any adverse reactions.

There is no specific antidote for ONCASPAR overdosage. In case of overdose, monitor patients closely for signs and symptoms of adverse reactions, and appropriately manage with symptomatic and supportive treatment.

11 DESCRIPTION

Pegaspargase is a conjugate of monomethoxypolyethylene glycol (mPEG) and L-asparaginase (L-asparagine amidohydrolase), an asparagine specific enzyme. L-asparaginase is a tetrameric enzyme that is produced endogenously by E. coli and consists of identical 34.5 kDa subunits. Approximately 69 to 82 molecules of mPEG are linked to L-asparaginase; the molecular weight of each mPEG molecule is about 5 kDa. ONCASPAR activity is expressed in International Units.

ONCASPAR (pegaspargase) injection is supplied as a clear, colorless, preservative-free, isotonic sterile solution in phosphate-buffered saline, pH 7.3, for intramuscular use or for dilution prior to intravenous infusion. Each vial of ONCASPAR contains 3,750 International Units of pegaspargase in 5 mL of solution. Each milliliter contains 750 International Units of pegaspargase, dibasic sodium phosphate, USP (5.58 mg), monobasic sodium phosphate, USP (1.20 mg), and Sodium Chloride, USP (8.50 mg) in Water for Injection, USP.

12 CLINICAL PHARMACOLOGY

12.1 Mechanism of Action

L-asparaginase is an enzyme that catalyzes the conversion of the amino acid L-asparagine into aspartic acid and ammonia. The pharmacological effect of ONCASPAR is thought to be based on the killing of leukemic cells due to depletion of plasma asparagine. Leukemic cells with low expression of asparagine synthetase have a reduced ability to synthesize asparagine, and therefore depend on an exogenous source of asparagine for survival.

12.2 Pharmacodynamics

Pharmacodynamic activity was assessed through serial measurements of asparagine in sera and cerebrospinal fluid (CSF).

In Study CCG-1962, pharmacodynamics were assessed in 57 newly diagnosed pediatric patients with standard-risk ALL who received three intramuscular doses of ONCASPAR (2,500 International Units/m^2), one each during induction and two delayed intensification treatment phases [see Clinical Studies (14.1)].

In Study AALL07P4, the pharmacodynamic response of pegaspargase was assessed in 47 evaluable patients with newly diagnosed high risk B-precursor ALL. Asparagine concentrations in plasma (N=42) were maintained below the assay limit of quantification for at least 11 days following a single dose of ONCASPAR 2,500 International Units/m^2 during the induction phase. CSF asparagine concentration was decreased from a mean pretreatment concentration of 0.6 µg/mL (N=20) to 0.2 µg/mL on Day 4 (N=41) and remained decreased at 0.2 µg/mL (N=39) 25 days after the administration of a single dose of ONCASPAR in the induction phase.

12.3 Pharmacokinetics

Pharmacokinetic assessments were based on an enzymatic assay measuring asparaginase activity after intramuscular (IM, CCG-1962) and intravenous (IV, AALL07P4) administration of 2,500 International Units/m^2 in patients with ALL.

Absorption

The mean maximum asparaginase activity (Cmax) was reached at approximately 1 IU/mL (n=45-52) on Day 5 after a single IM injection. The mean half-life of absorption from the IM site was 1.7 days. The relative bioavailability was 82% following the first IM dose and 98% following repeat dosing.

The mean Cmax and the area under the curve (AUC0-inf) was 1.6 IU/mL and 16.6 IU/mL*day, respectively, after a single IV infusion (n=47) during the induction phase.

Distribution

The mean volume of distribution at steady state was estimated to be 1.86 L/m^2 after a single IM injection and approximately 2 L after a single IV infusion based on non-compartmental analysis.

Elimination

The mean elimination half-life was approximately 5.8 days following a single IM injection and 5.3 days following a single IV infusion. The clearance was 0.17 L/m^2/day and 0.2 L/day, respectively, for a single IM and IV dose.

Specific Populations

The impact of renal and hepatic impairment on the pharmacokinetics of ONCASPAR is unknown.

13 NONCLINICAL TOXICOLOGY

13.1 Carcinogenesis, Mutagenesis, Impairment of Fertility

Carcinogenicity, mutagenicity and impairment of fertility studies have not been conducted with pegaspargase.

14 CLINICAL STUDIES

14.1 First-Line Treatment of ALL

Study CCG-1962

The safety and effectiveness of ONCASPAR was evaluated in an open label, multicenter, randomized, active controlled study (Study CCG-1962). In this study, 118 pediatric patients aged 1 to 9 years with previously untreated standard-risk ALL were randomized 1:1 to ONCASPAR or native E. coli L-asparaginase as part of combination therapy. ONCASPAR was administered intramuscularly at a dose of 2,500 International Units/m^2 on Day 3 of the 4 week induction phase and on Day 3 of each of two 8 week delayed intensification phases. Native E. coli L-asparaginase was administered intramuscularly at a dose of 6,000 International Units/m^2 three times weekly for 9 doses during induction and for 6 doses during each delayed intensification phase.

The primary determination of effectiveness was based on demonstration of similar asparagine depletion (magnitude and duration) in the ONCASPAR and native E. coli L-asparaginase arms. The protocol-specified goal was achievement of asparagine depletion to a serum concentration of ≤1 µM. The proportion of patients with this level of depletion was similar between the 2 study arms during all 3 phases of treatment at the protocol-specified time points.

In all phases of treatment, serum asparagine concentrations decreased within 4 days of the first dose of asparaginase in the treatment phase and remained low for approximately 3 weeks for both ONCASPAR and native E. coli L-asparaginase arms. Serum asparagine concentrations during the induction phase are shown in Figure 1. The patterns of serum asparagine depletion in the 2 delayed intensification phases are similar to the pattern of serum asparagine depletion in the induction phase.

Figure 1. Mean (± Standard Error) Serum Asparagine Concentrations During Study CCG-1962 Induction Phase

Note: ONCASPAR (2,500 International Units/m^2 intramuscular) was administered on Day 3 of the 4-week induction phase. Native E. coli L-asparaginase (6,000 International Units/m^2 intramuscular) was administered 3 times weekly for 9 doses during induction.

CSF asparagine concentrations were determined in 50 patients during the induction phase. CSF asparagine decreased from a mean pre-treatment concentration of 3.1 µM to 1.7 µM on Day 4±1 and 1.5 µM at 25±1 days after administration of ONCASPAR. These findings were similar to those observed in the native E. coli L-asparaginase treatment arm.

Concentrations of asparaginase activities greater than 0.1 International Units/mL were observed in over 90% of the samples from patients treated with ONCASPAR during Induction, Delayed Intensification 1, and Delayed Intensification 2 for approximately 20 days.

While the 3-year Event-Free Survival (EFS) for the ONCASPAR and native E. coli L-asparaginase study arms were similar and in the range of 80%, Study CCG-1962 was not designed to evaluate for differences in EFS rates.

14.2 Patients with ALL Hypersensitive to Asparaginase

The safety and effectiveness of ONCASPAR was evaluated in 4 open label studies enrolling a total of 42 patients with multiply relapsed, acute leukemia [39 (93%) with ALL] with a history of prior clinical allergic reaction to asparaginase. Hypersensitivity to asparaginase was defined by a history of systemic rash, urticaria, bronchospasm, laryngeal edema, hypotension, or local erythema, urticaria, or swelling, greater than 2 centimeters, for at least 10 minutes following administration of any form of native E. coli L-asparaginase. All patients received ONCASPAR at a dose of 2,000 or 2,500 International Units/m^2 administered intramuscularly or intravenously every 14 days. Patients received ONCASPAR as a single agent or in combination with multi-agent chemotherapy. The re-induction response rate was 50% (95% confidence interval: 35%, 65%), based upon 36% complete remissions and 14% partial remissions. These results were similar to the overall response rates reported for patients with ALL receiving second-line, native E. coli L-asparaginase-containing re-induction chemotherapy. Anti-tumor activity was also observed with single-agent ONCASPAR. Three responses (1 complete remission and 2 partial remissions) were observed in 9 adult and pediatric patients with relapsed ALL and hypersensitivity to native E. coli L-asparaginase.

16 HOW SUPPLIED/STORAGE AND HANDLING

ONCASPAR (pegaspargase) injection is supplied as a sterile, clear, colorless, preservative-free solution in Type I single-dose vial containing 3,750 International Units of pegaspargase per 5 mL (750 International Units per mL) solution (NDC 72694-954-01).

STORAGE AND HANDLING

Store ONCASPAR refrigerated at 2°C to 8°C (36°F to 46°F) in the original carton to protect from light. Do not shake or freeze product. Unopened vials may be stored at room temperature (15°C to 25°C [59°F to 77°F]) for no more than 48 hours.

17 PATIENT COUNSELING INFORMATION

Anaphylaxis and Serious Hypersensitivity Reactions

Inform patients of the possibility of serious allergic reactions, including anaphylaxis, and to seek immediate medical care for any swellings or difficulty breathing [see Warnings and Precautions (5.1)].

Thrombosis

Instruct patients on the risk of thrombosis and hemorrhage and to seek immediate medical attention if they experience severe headache, arm or leg swelling, shortness of breath, or chest pain [see Warnings and Precautions (5.2)].

Pancreatitis

Instruct patients on the signs and symptoms of pancreatitis and to seek immediate medical attention if they experience severe abdominal pain [see Warnings and Precautions (5.3)].

Glucose Intolerance

Instruct patients on the risk of hyperglycemia and glucose intolerance. Advise patients to immediately report excessive thirst or increase in the volume or frequency of urination [see Warnings and Precautions (5.4)].

Hemorrhage

Advise patients to report any unusual bleeding or bruising to their healthcare provider [see Warnings and Precautions (5.5)].

Hepatotoxicity, including Veno-Occlusive Liver Disease (VOD)

Inform patients that liver problems, including severe, life-threatening, or fatal VOD and abnormalities in liver tests, may develop during ONCASPAR treatment. Advise patients to contact their healthcare provider immediately if they experience jaundice, rapid weight gain, abdominal swelling, or right upper abdominal pain or tenderness [see Warnings and Precautions (5.6)].

Pregnancy

Advise pregnant women of the potential risk to a fetus. Advise females of reproductive potential to inform their healthcare provider of a known or suspected pregnancy [see Use in Specific Populations (8.1)].

Advise females of reproductive potential to use effective non-hormonal contraception during treatment with ONCASPAR and for 3 months after the last dose [see Use in Specific Populations (8.3)].

Lactation

Advise women not to breastfeed during treatment with ONCASPAR and for 1 month after the last dose [see Use in Specific Populations (8.2)].

ONCASPAR is a registered trademark of Servier IP UK LTD, a wholly owned, indirect subsidiary of Les Laboratoires Servier.

Servier and the Servier logo are trademarks of Les Laboratoires Servier.

Manufactured by: Servier Pharmaceuticals LLC, Boston, MA 02210
U.S. License No. 2125

PRINCIPAL DISPLAY PANEL - 5 mL Vial Carton

NDC 72694-954-01

ONCASPAR®
pegaspargase
Injection

3750 International
Units Per 5 mL
(750 International
Units Per mL)

For intravenous or intramuscular use.

Single-use vial.

Discard unused portion.

Rx ONLY
SERVIER